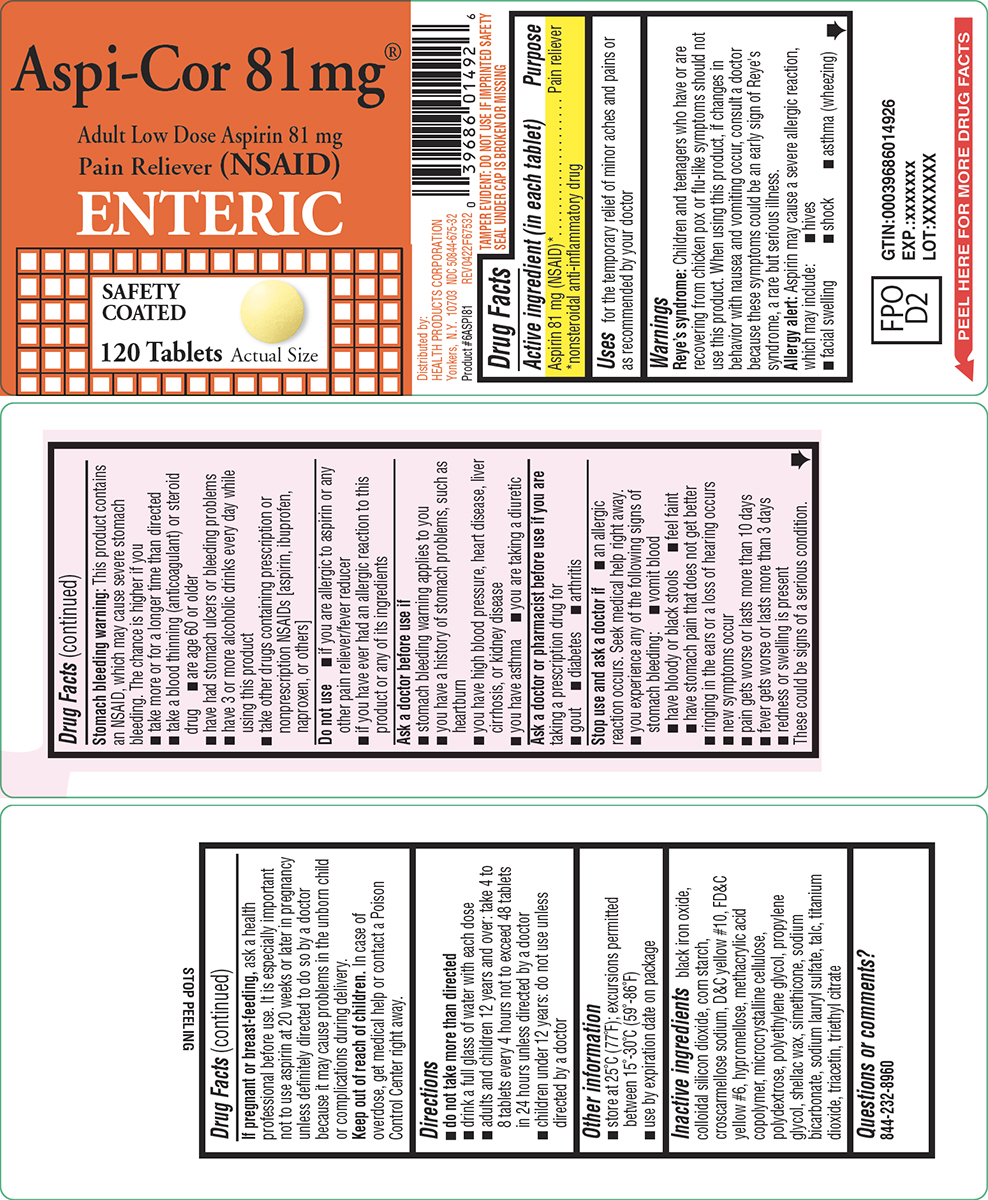 DRUG LABEL: Aspi-Cor
NDC: 50844-675 | Form: TABLET, DELAYED RELEASE
Manufacturer: L.N.K. International, Inc.
Category: otc | Type: HUMAN OTC DRUG LABEL
Date: 20250808

ACTIVE INGREDIENTS: ASPIRIN 81 mg/1 1
INACTIVE INGREDIENTS: FERROSOFERRIC OXIDE; SILICON DIOXIDE; STARCH, CORN; CROSCARMELLOSE SODIUM; D&C YELLOW NO. 10; FD&C YELLOW NO. 6; HYPROMELLOSE, UNSPECIFIED; METHACRYLIC ACID AND ETHYL ACRYLATE COPOLYMER; MICROCRYSTALLINE CELLULOSE; POLYDEXTROSE; POLYETHYLENE GLYCOL, UNSPECIFIED; PROPYLENE GLYCOL; SHELLAC; DIMETHICONE; WATER; SODIUM BICARBONATE; SODIUM LAURYL SULFATE; TALC; TITANIUM DIOXIDE; TRIACETIN; TRIETHYL CITRATE

Aspi-Cor 44-675

Active ingredient (in each tablet)

Aspirin 81 mg (NSAID)*
*nonsteroidal anti-inflammatory drug

Purpose

Pain reliever

Uses

for the temporary relief of minor aches and pains or as recommended by your doctor

Warnings

Reye’s syndrome: Children and teenagers who have or are recovering from chicken pox or flu-like symptoms should not use this product. When using this product, if changes in behavior with nausea and vomiting occur, consult a doctor because these symptoms could be an early sign of Reye's syndrome, a rare but serious illness.

Allergy alert: Aspirin may cause a severe allergic reaction, which may include:

- hives
- facial swelling
- shock
- asthma (wheezing)

Stomach bleeding warning: This product contains an NSAID, which may cause severe stomach bleeding. The chance is higher if you

- are age 60 or older
- take more or for a longer time than directed
- take a blood thinning (anticoagulant) or steroid drug
- have had stomach ulcers or bleeding problems
- have 3 or more alcoholic drinks every day while using this product
- take other drugs containing prescription or nonprescription NSAIDs [aspirin, ibuprofen, naproxen, or others]

Do not use

- if you are allergic to aspirin or any other pain reliever/fever reducer
- if you have ever had an allergic reaction to this product or any of its ingredients

Ask a doctor before use if

- stomach bleeding warning applies to you
- you have a history of stomach problems, such as heartburn
- you have high blood pressure, heart disease, liver cirrhosis, or kidney disease
- you have asthma
- you are taking a diuretic

Ask a doctor or pharmacist before use if you are

taking a prescription drug for

- gout
- diabetes
- arthritis

Stop use and ask a doctor if

- an allergic reaction occurs. Seek medical help right away.
- you experience any of the following signs of stomach bleeding:
  - vomit blood
  - have bloody or black stools
  - feel faint
  - have stomach pain that does not get better
- ringing in the ears or a loss of hearing occurs
- new symptoms occur
- pain gets worse or lasts more than 10 days
- fever gets worse or lasts more than 3 days
- redness or swelling is present

These could be signs of a serious condition.

If pregnant or breast-feeding,

ask a health professional before use. It is especially important not to use aspirin at 20 weeks or later in pregnancy unless definitely directed to do so by a doctor because it may cause problems in the unborn child or complications during delivery.

Keep out of reach of children.

In case of overdose, get medical help or contact a Poison Control Center right away.

Directions

- do not take more than directed
- drink a full glass of water with each dose
- adults and children 12 years and over: take 4 to 8 tablets every 4 hours not to exceed 48 tablets in 24 hours unless directed by a doctor
- children under 12 years: do not use unless directed by a doctor

Other information

- store at 25ºC (77ºF); excursions permitted between 15º-30ºC (59º-86ºF)
- use by expiration date on package

Inactive ingredients

black iron oxide, colloidal silicon dioxide, corn starch, croscarmellose sodium, D&C yellow #10, FD&C yellow #6, hypromellose, methacrylic acid copolymer, microcrystalline cellulose, polydextrose, polyethylene glycol, propylene glycol, shellac wax, simethicone, sodium bicarbonate, sodium lauryl sulfate, talc, titanium dioxide, triacetin, triethyl citrate

Questions or comments?

844-232-8960

Principal display panel

Aspi-Cor 81 mg®

Adult Low Dose Aspirin 81 mg
Pain Reliever (NSAID)

ENTERIC

SAFETY
COATED

120 Tablets

Actual Size

Distributed by:
HEALTH PRODUCTS CORPORATION
Yonkers, N.Y. 10703 NDC 50844-675-32
Product #6ASPI81 REV0422F67532

TAMPER EVIDENT: DO NOT USE IF IMPRINTED SAFETY
SEAL UNDER CAP IS BROKEN OR MISSING

Aspi-Cor 44-675